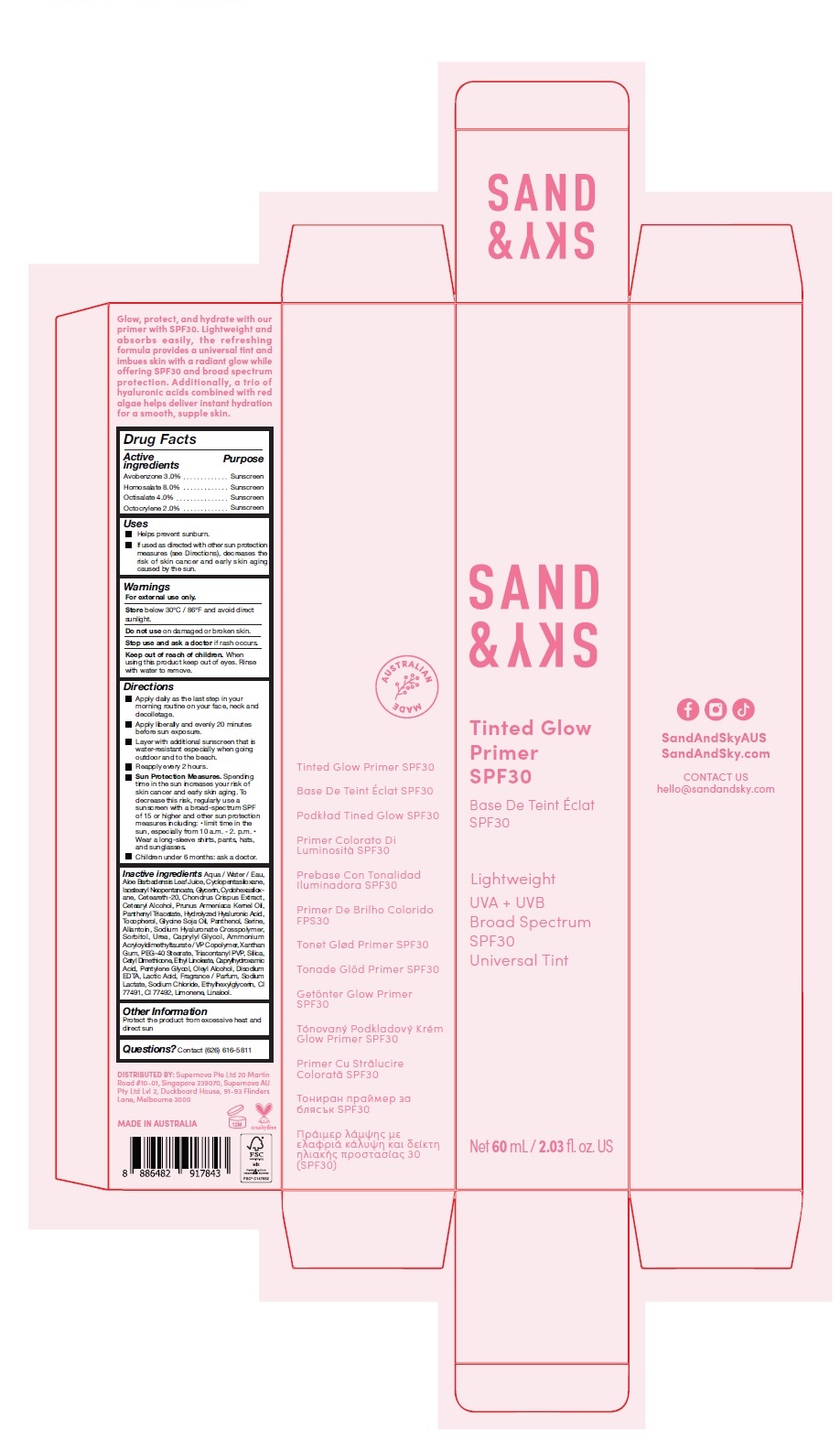 DRUG LABEL: SAND AND SKY TINTED GLOW PRIMER SPF30
NDC: 82931-001 | Form: LOTION
Manufacturer: Supernova USA Inc.
Category: otc | Type: HUMAN OTC DRUG LABEL
Date: 20220829

ACTIVE INGREDIENTS: AVOBENZONE 3 g/100 mL; HOMOSALATE 8 g/100 mL; OCTISALATE 4 g/100 mL; OCTOCRYLENE 2 g/100 mL
INACTIVE INGREDIENTS: WATER; ALOE VERA LEAF; CYCLOMETHICONE 5; ISOSTEARYL NEOPENTANOATE; GLYCERIN; CYCLOMETHICONE 6; POLYOXYL 20 CETOSTEARYL ETHER; CHONDRUS CRISPUS CARRAGEENAN; CETOSTEARYL ALCOHOL; APRICOT KERNEL OIL; PANTHENOL TRIACETATE, (+)-; HYALURONIC ACID; TOCOPHEROL; SOYBEAN OIL; PANTHENOL; SERINE; ALLANTOIN; HYALURONATE SODIUM; SORBITOL; UREA; CAPRYLYL GLYCOL; AMMONIUM ACRYLOYLDIMETHYLTAURATE/VP COPOLYMER; XANTHAN GUM; PEG-40 STEARATE; TRICONTANYL POVIDONE; SILICON DIOXIDE; CETYL DIMETHICONE 25; ETHYL LINOLEATE; CAPRYLHYDROXAMIC ACID; PENTYLENE GLYCOL; OLEYL ALCOHOL; EDETATE DISODIUM ANHYDROUS; LACTIC ACID, UNSPECIFIED FORM; SODIUM LACTATE; SODIUM CHLORIDE; ETHYLHEXYLGLYCERIN; FERRIC OXIDE RED; FERRIC OXIDE YELLOW; LIMONENE, (+)-; LINALOOL, (+/-)-

SAND & SKY TINTED GLOW PRIMER SPF30

Drug Facts

ACTIVE INGREDIENT

PURPOSE

Active
Ingredients Purpose

Avobenzone 3.0% Sunscreen

Homosalate 8.0% Sunscreen

Octisalate 4.0% Sunscreen

Octocrylene 2.0% Sunscreen

Uses

- Helps prevent sunburn.
- If used as directed with other sun protection measures (see Directions), decreases the risk of skin cancer and early skin aging caused by the sun.

Warnings

For external use only.

DO NOT USE

Store below 30°C / 86°F and avoid direct sunlight.

Do not use on damaged or broken skin.

Stop use and ask a doctor if rash occurs.

Keep out of reach of children. When using this product keep out of eyes. Rinse with water to remove.

Directions

- Apply daily as the last step in your morning routine on your face, neck and decolletage.
- Apply liberally and evenly 20 minutes before sun exposure.
- Layer with additional sunscreen that is water-resistant especially when going outdoor and to the beach.
- Reapply every 2 hours.
- Sun Protection Measures. Spending time in the sun increases your risk of skin cancer and early skin aging. To decrease this risk, regularly use a sunscreen with a broad-spectrum SPF of 15 or higher and other sun protection measures including:
  - limit time in the sun, especially from 10 a.m. - 2. p.m.
  - Wear a long-sleeve shirts, pants, hats, and sunglasses.
- Children under 6 months: ask a doctor.

INACTIVE INGREDIENT

Inactive ingredients Aqua / Water / Eau, Aloe Barbadensis Leaf Juice, Cyclopentasiloxane, Isostearyl Neopentanoate, Glycerin, Cyclohexasiloxane, Ceteareth-20, Chondrus Crispus Extract, Cetearyl Alcohol, Prunus Armeniaca Kernel Oil, Panthenyl Triacetate, Hydrolyzed Hyaluronic Acid, Tocopherol, Glycine Soja Oil, Panthenol, Serine, Allantoin, Sodium Hyaluronate Crosspolymer, Sorbitol, Urea, Caprylyl Glycol, Ammonium Acryloyldimethyltaurate / VP Copolymer, Xanthan Gum, PEG-40 Stearate, Triacontanyl PVP, Silica, Cetyl Dimethicone, Ethyl Linoleate, Caprylhydroxamic Acid, Pentylene Glycol, Oleyl Alcohol, Disodium EDTA, Lactic Acid, Fragrance / Parfum, Sodium Lactate, Sodium Chloride, Ethylhexylglycerin, CI 77491, CI 77492, Limonene, Linalool.

Other information

Protect the product from excessive heat and direct sun

STORAGE AND HANDLING

Questions? Contact (626) 616-5811

PRINCIPAL DISPLAY PANEL - 60 mL Tube Carton

SAND & SKY

Tinted Glow
Primer
SPF30

Base De Teint Éclat
SPF30

Lightweight

UVA + UVB
Broad Spectrum
SPF30
Universal Tint

Net 60 mL / 2.03 fl. oz. US